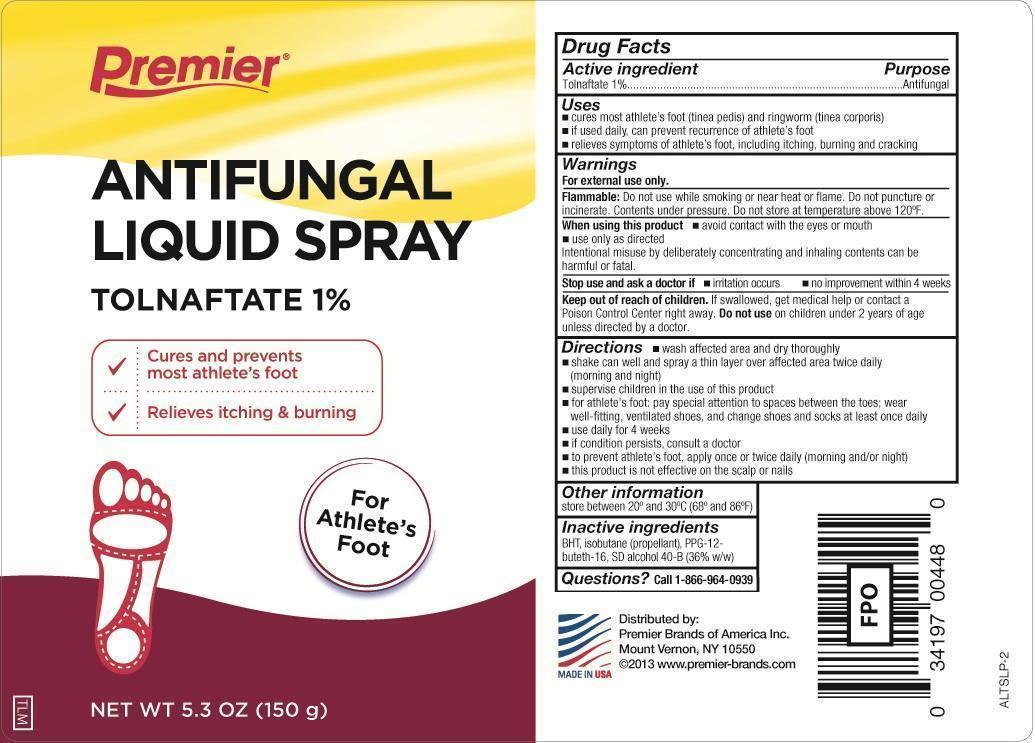 DRUG LABEL: Tolnaftate
NDC: 56104-001 | Form: AEROSOL, SPRAY
Manufacturer: Premier Brands of America Inc.
Category: otc | Type: HUMAN OTC DRUG LABEL
Date: 20251031

ACTIVE INGREDIENTS: TOLNAFTATE 1.5 g/150 g
INACTIVE INGREDIENTS: ALCOHOL; BUTYLATED HYDROXYTOLUENE; ISOBUTANE; PPG-12-BUTETH-16

Premier Brands Tolnaftate Liquid Spray

Active ingredient

Tolnaftate 1%

Purpose

Antifungal

Uses

- cures most athlete's foot (tinea pedis) and ringworm (tinea corporis)
- if used daily, can prevent recurrence of athlete's foot
- relieves sypmtoms of athlete's foot, including itching, burning and cracking

Warnings

For external use only.

Flammable:

Do not use while smoking or near heat or flame. Do not puncture or incinerate. Contents under pressure. Do not store at temperature above 120ºF

When using this product

- avoid contact with the eyes or mouth
- use only as directed

Intentional misuse by deliberately concentrating and inhaling contents cans be harmful or fatal.

Stop use and ask a doctor if

- irritation occurs
- no improvement within 4 weeks

Keep out of reach of children.

If swallowed, get medical help or contact a Poison Control Center right away. Do not use on children under 2 years of age unless directed by a doctor.

Directions

- wash affected area and dry thoroughly
- shake can well and spray a thin layer over affected area twice daily (morning and night)
- supervise children in the use of this product
- for athlete's foot: pay special attention to spaces between the toes; wear well-fitting, ventilated shoes, and change shoes and socks at least once daily
- use daily for 4 weeks
- if conditions persist, consult a doctor
- to prevent athlete's foot, apply once or twice daily (morning and/or night)
- this product is not effective on the scalp or nails

Other information

store between 20º and 30ºC (68ºF and 86º)

Inactive ingredients

BHT, isobutane (propellant), PPG-12-buteth-16, SD alcohol 40-B(36%w/w)

Questions

Call 1-866-964-0939

Principal Display Panel

Premier

Athlete's Foot

Antifungal Liquid Spray

Tolnaftate 1%

- Cures and prevents most athlete's foot
- Relieves itching & burning

For Athlete's Foot

NET WT 5.3oz(150g)